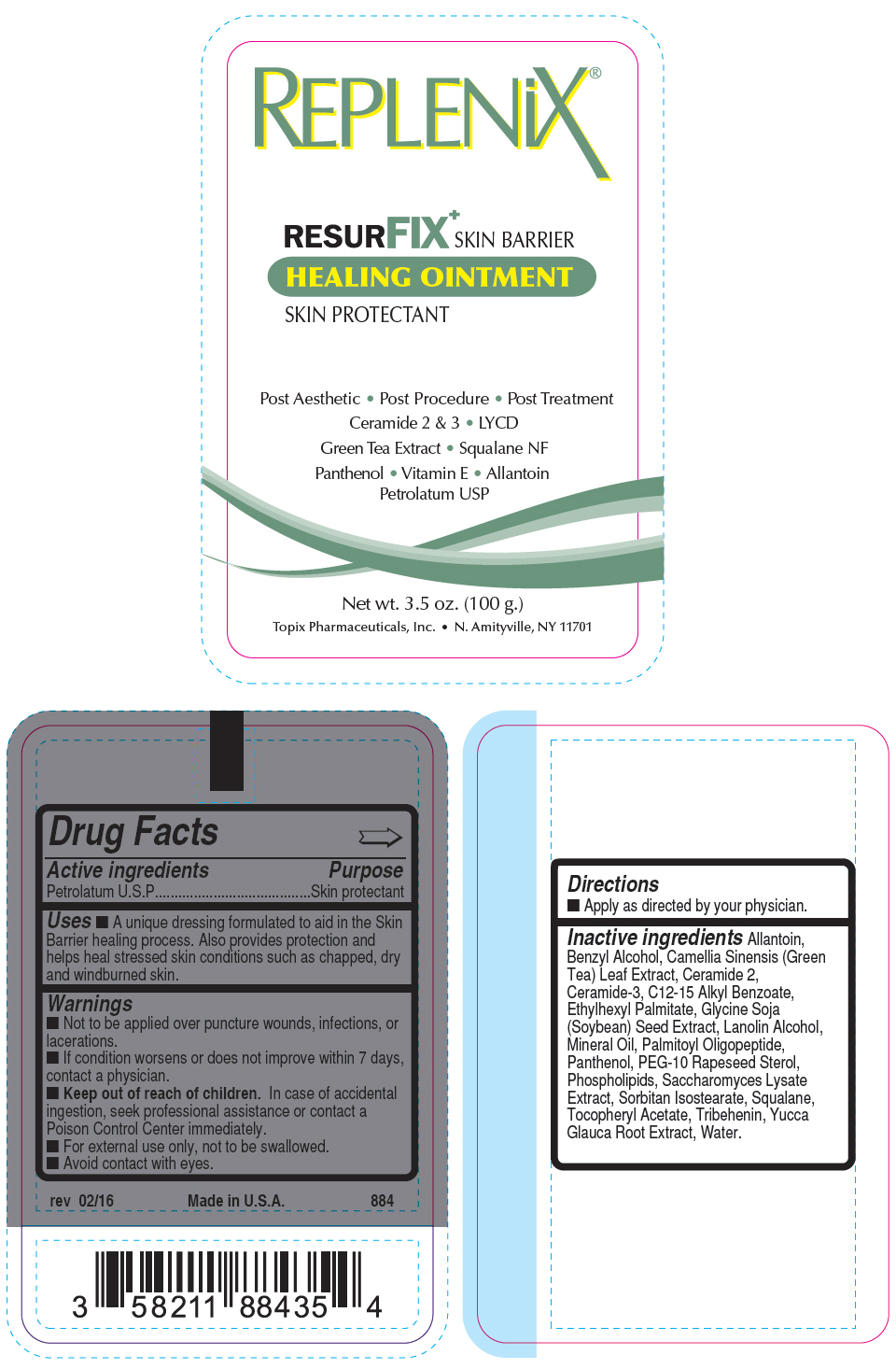 DRUG LABEL: Resurfix Plus
NDC: 51326-884 | Form: OINTMENT
Manufacturer: Topiderm, Inc.
Category: otc | Type: HUMAN OTC DRUG LABEL
Date: 20191119

ACTIVE INGREDIENTS: PETROLATUM 86 mg/1 g
INACTIVE INGREDIENTS: ALLANTOIN; BENZYL ALCOHOL; GREEN TEA LEAF; CERAMIDE NG; CERAMIDE NP; ALKYL (C12-15) BENZOATE; ETHYLHEXYL PALMITATE; SOYBEAN; LANOLIN ALCOHOLS; MINERAL OIL; PALMITOYL TRIPEPTIDE-1; PANTHENOL; PEG-10 RAPESEED STEROL; LECITHIN, SOYBEAN; SACCHAROMYCES LYSATE; SORBITAN ISOSTEARATE; SQUALANE; .ALPHA.-TOCOPHEROL ACETATE; TRIBEHENIN; YUCCA GLAUCA ROOT; WATER

Resurfix Ointment Plus

Drug Facts

Active ingredients

Petrolatum U.S.P

Purpose

Skin protectant

Uses

- A unique dressing formulated to aid in the Skin Barrier healing process. Also provides protection and helps heal stressed skin conditions such as chapped, dry and windburned skin.

Warnings

- Not to be applied over puncture wounds, infections, or lacerations.
- If condition worsens or does not improve within 7 days, contact a physician.

- Keep out of reach of children. In case of accidental ingestion, seek professional assistance or contact a Poison Control Center immediately.

- For external use only, not to be swallowed.
- Avoid contact with eyes.

Directions

- Apply as directed by your physician.

Inactive ingredients

Allantoin, Benzyl Alcohol, Camellia Sinensis (Green Tea) Leaf Extract, Ceramide 2, Ceramide-3, C12-15 Alkyl Benzoate, Ethylhexyl Palmitate, Glycine Soja (Soybean) Seed Extract, Lanolin Alcohol, Mineral Oil, Palmitoyl Oligopeptide, Panthenol, PEG-10 Rapeseed Sterol, Phospholipids, Saccharomyces Lysate Extract, Sorbitan Isostearate, Squalane, Tocopheryl Acetate, Tribehenin, Yucca Glauca Root Extract, Water.

PRINCIPAL DISPLAY PANEL - 100 g Tube Label

REPLENiX®

RESURFIX^+SKIN BARRIER
HEALING OINTMENT
SKIN PROTECTANT

Post Aesthetic • Post Procedure • Post Treatment
Ceramide 2 & 3 • LYCD
Green Tea Extract • Squalane NF
Panthenol • Vitamin E • Allantoin
Petrolatum USP

Net wt. 3.5 oz. (100 g.)
Topix Pharmaceuticals, Inc. • N. Amityville, NY 11701